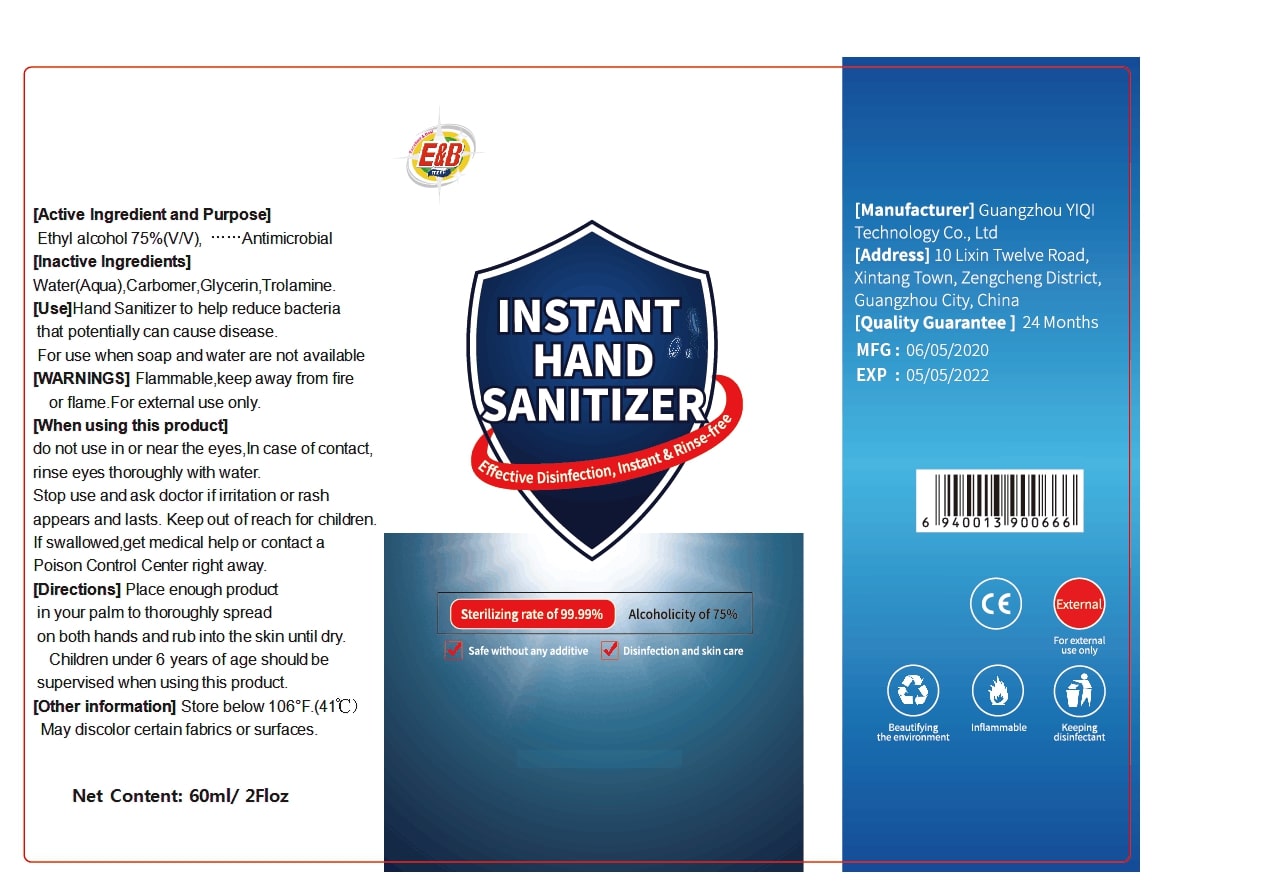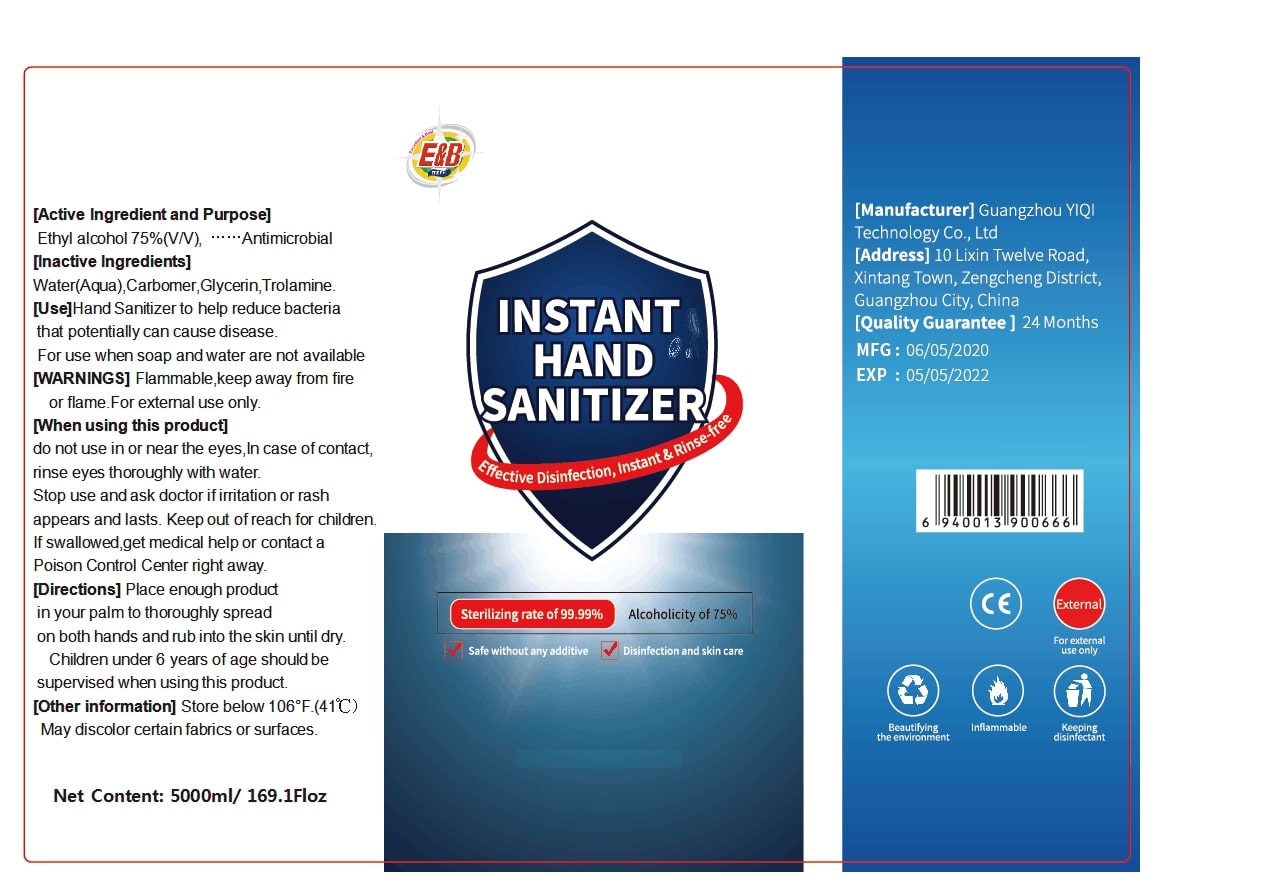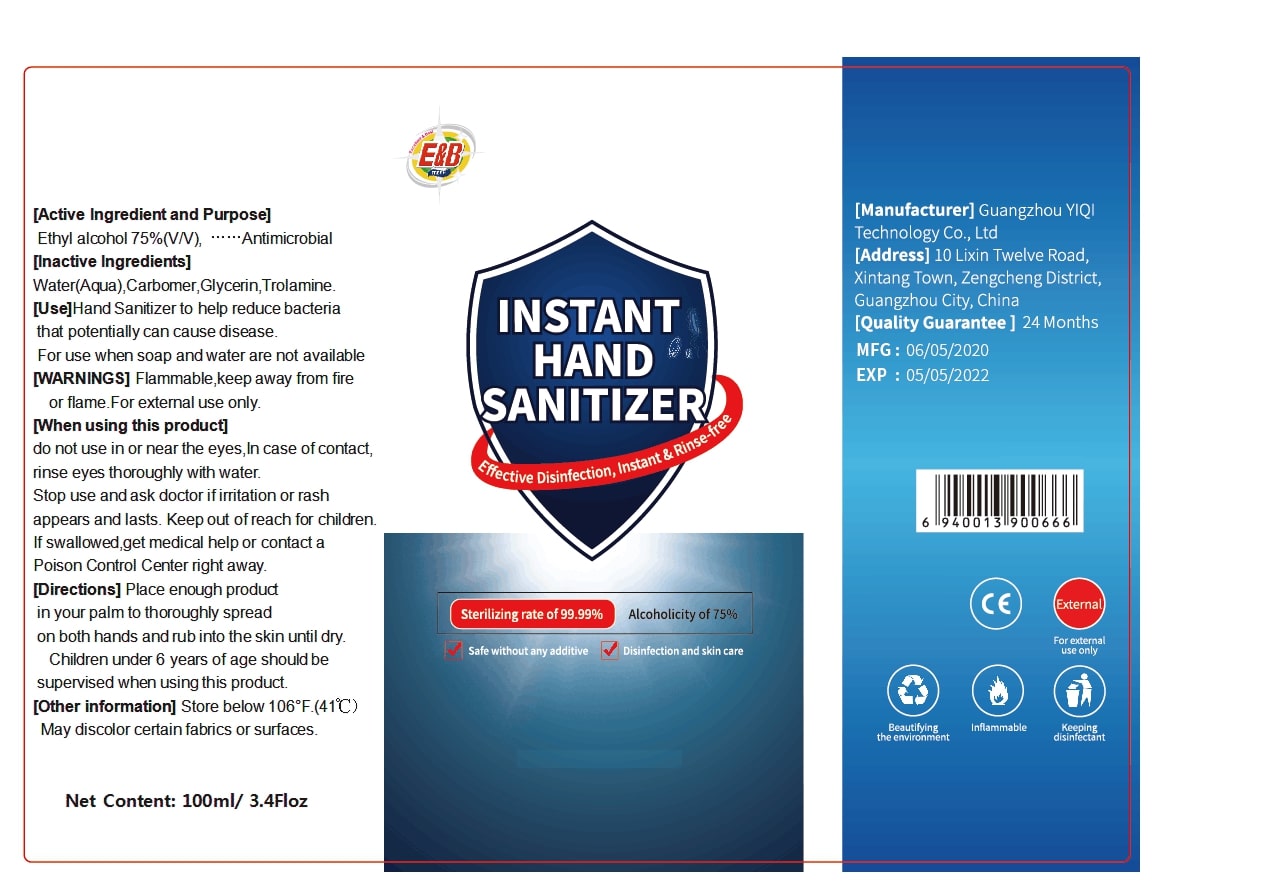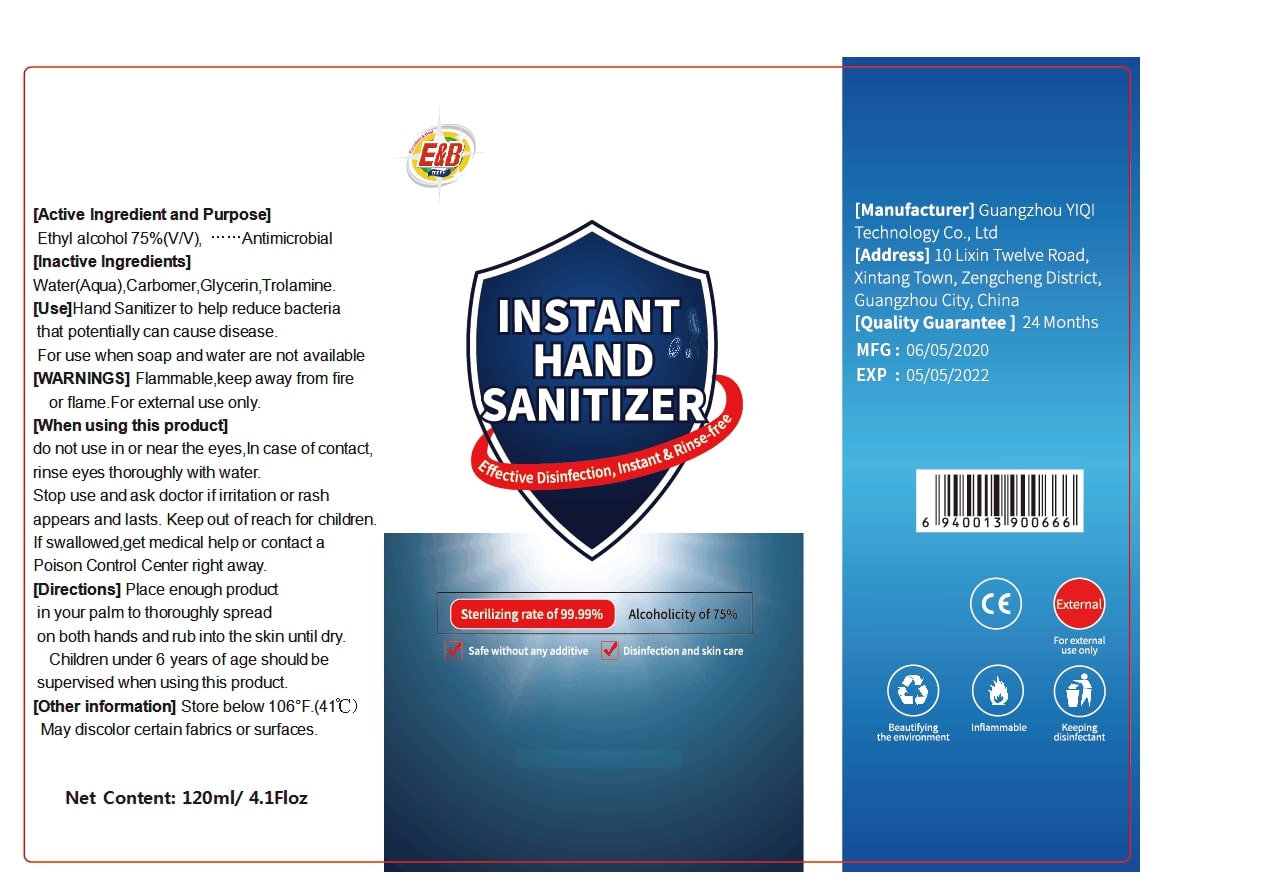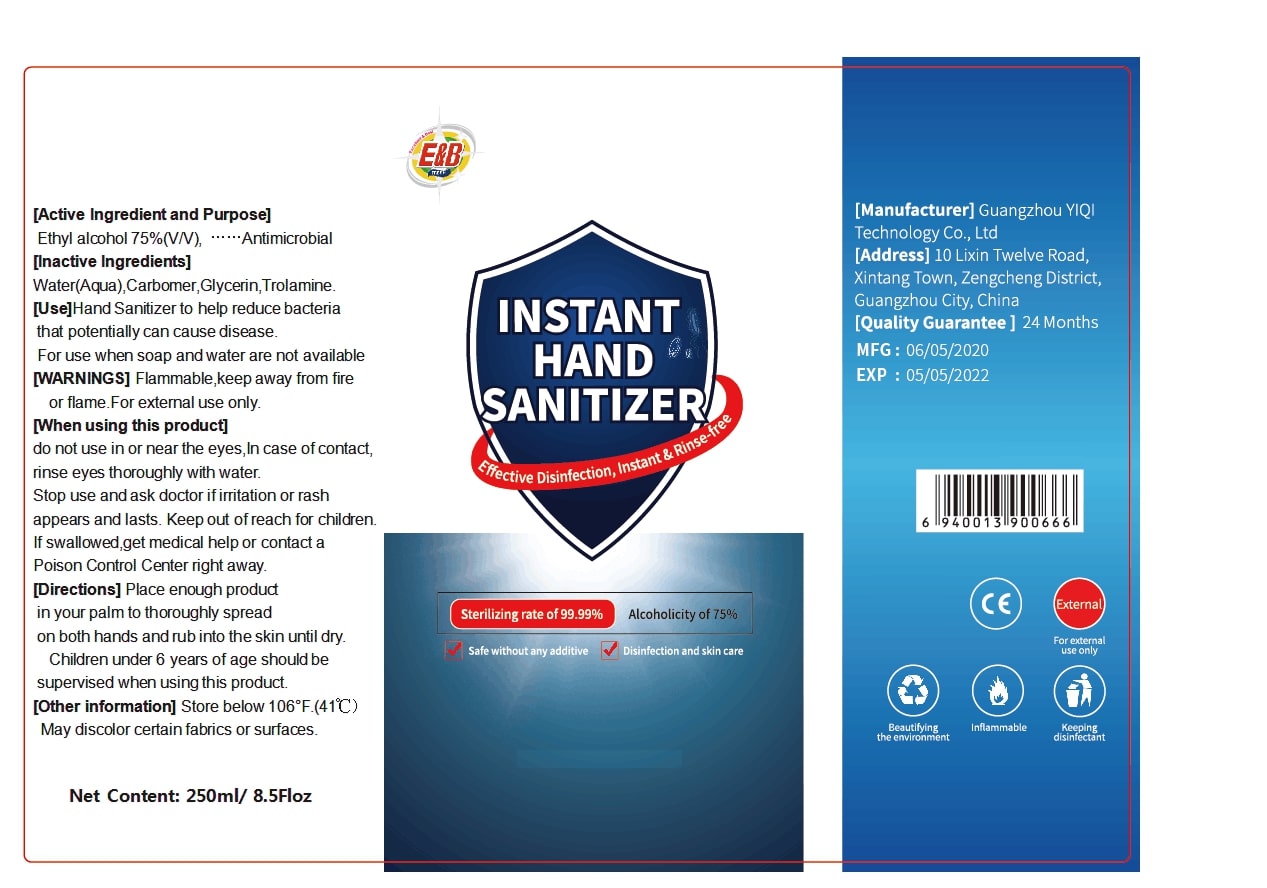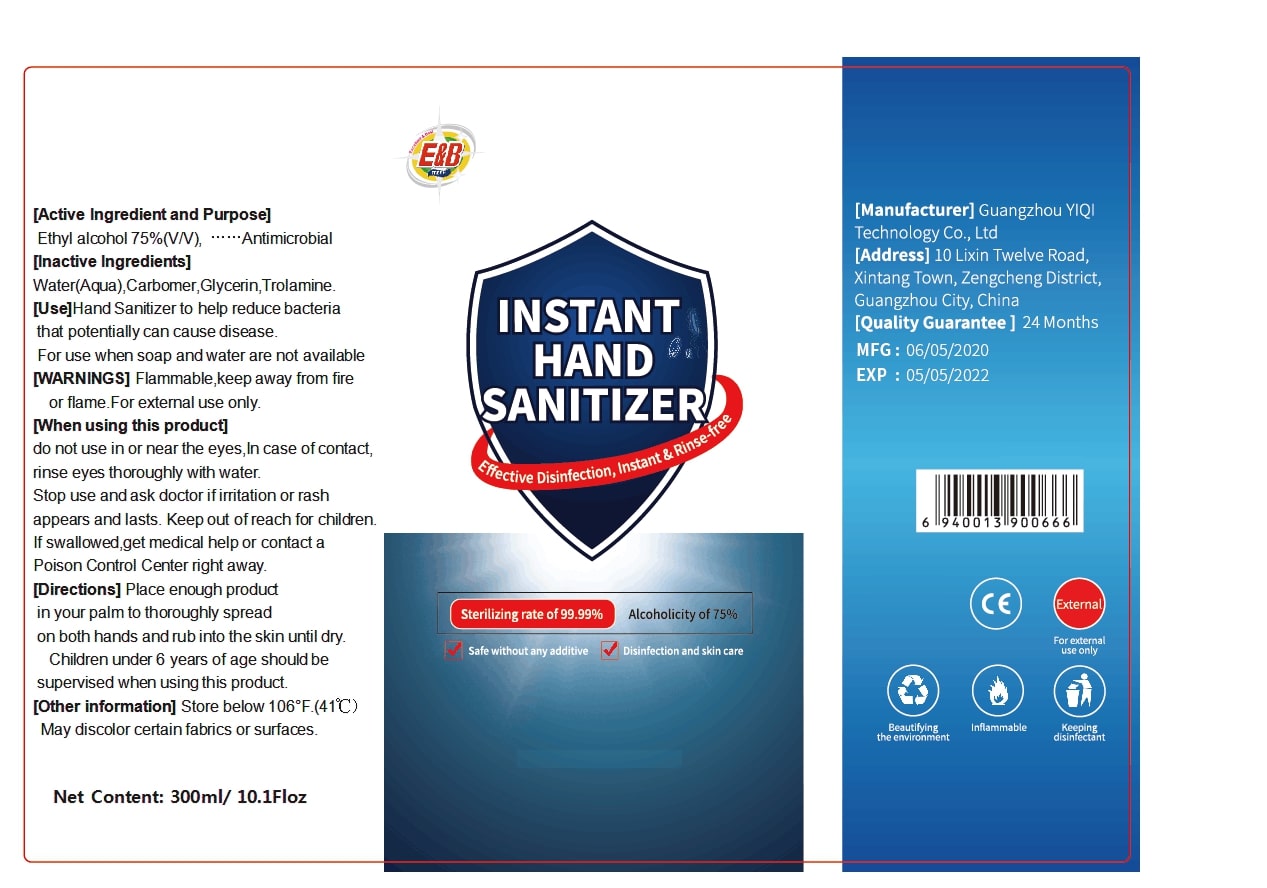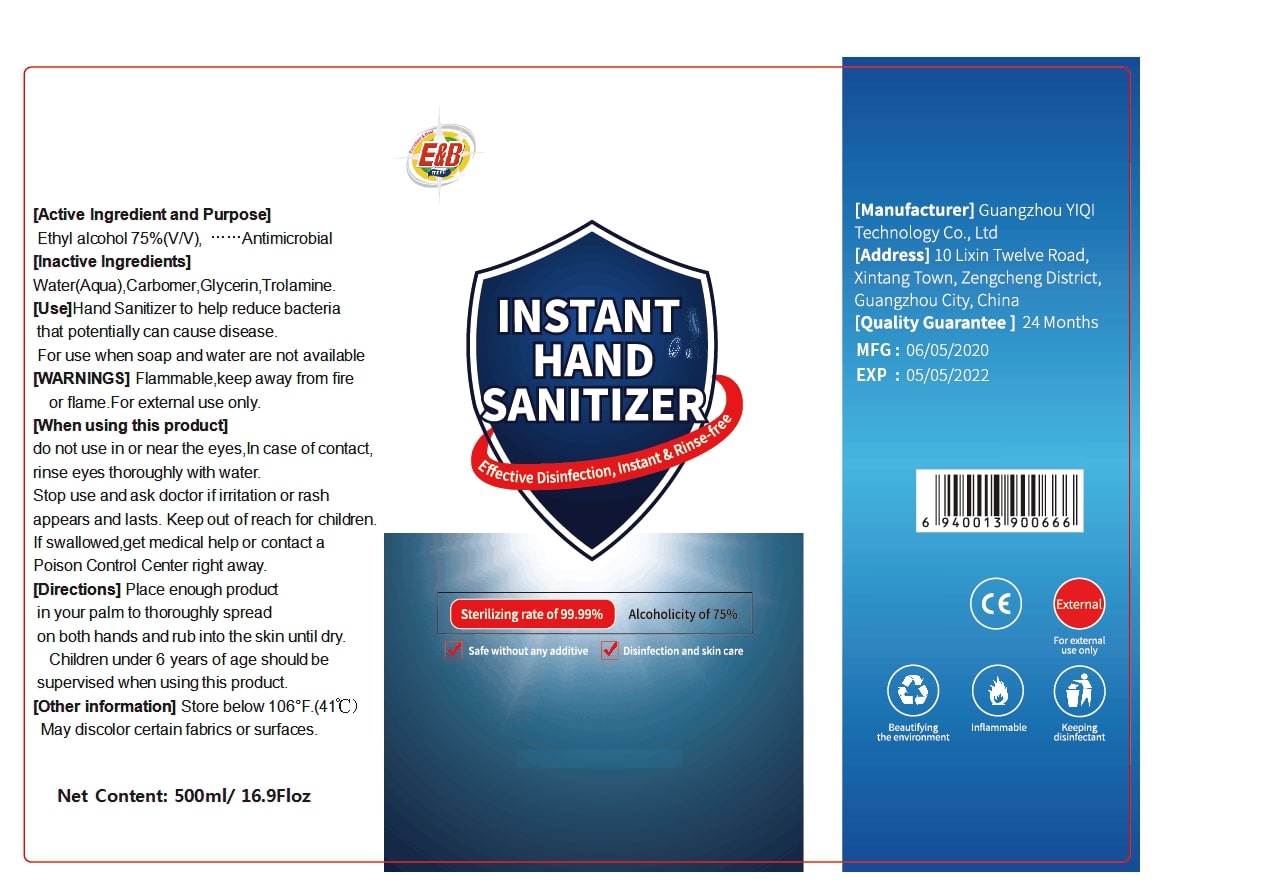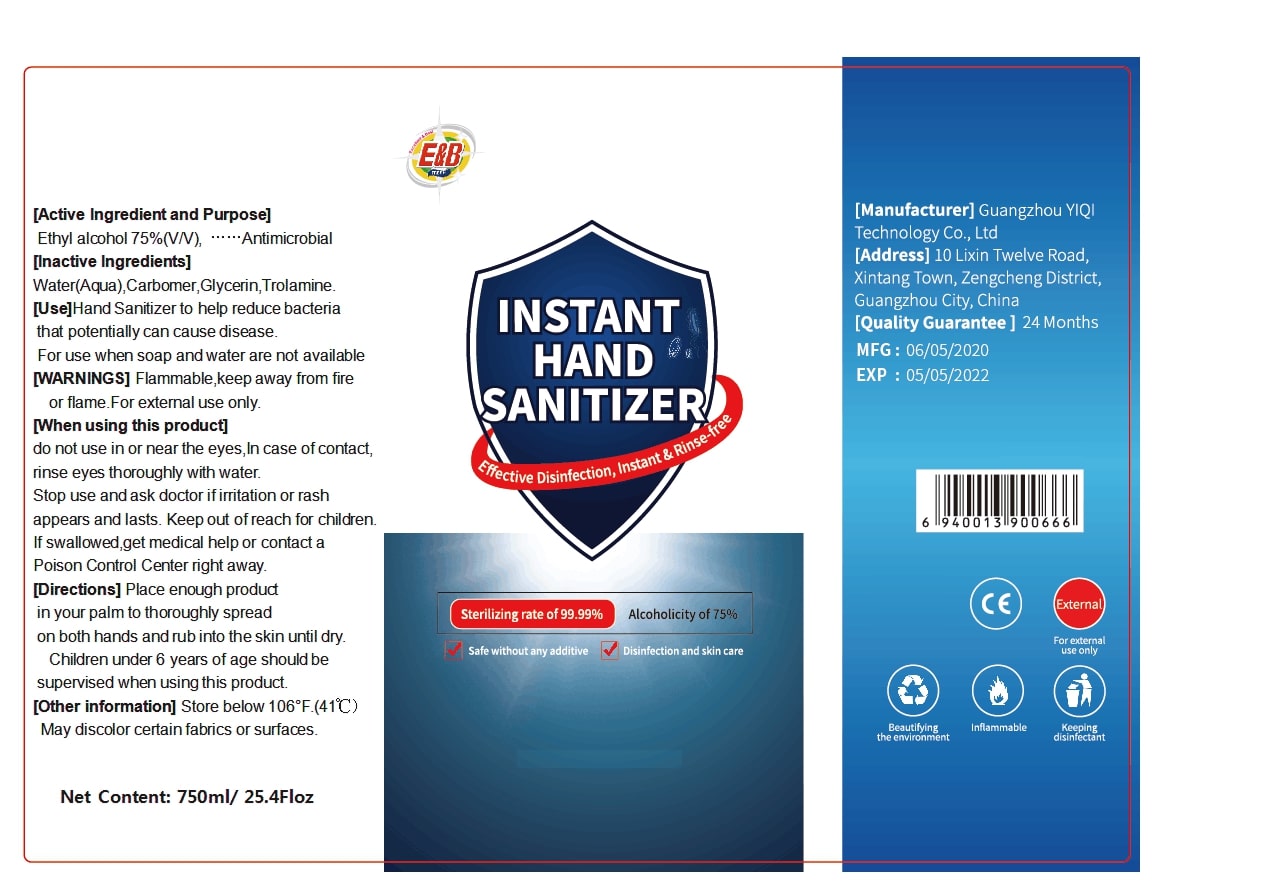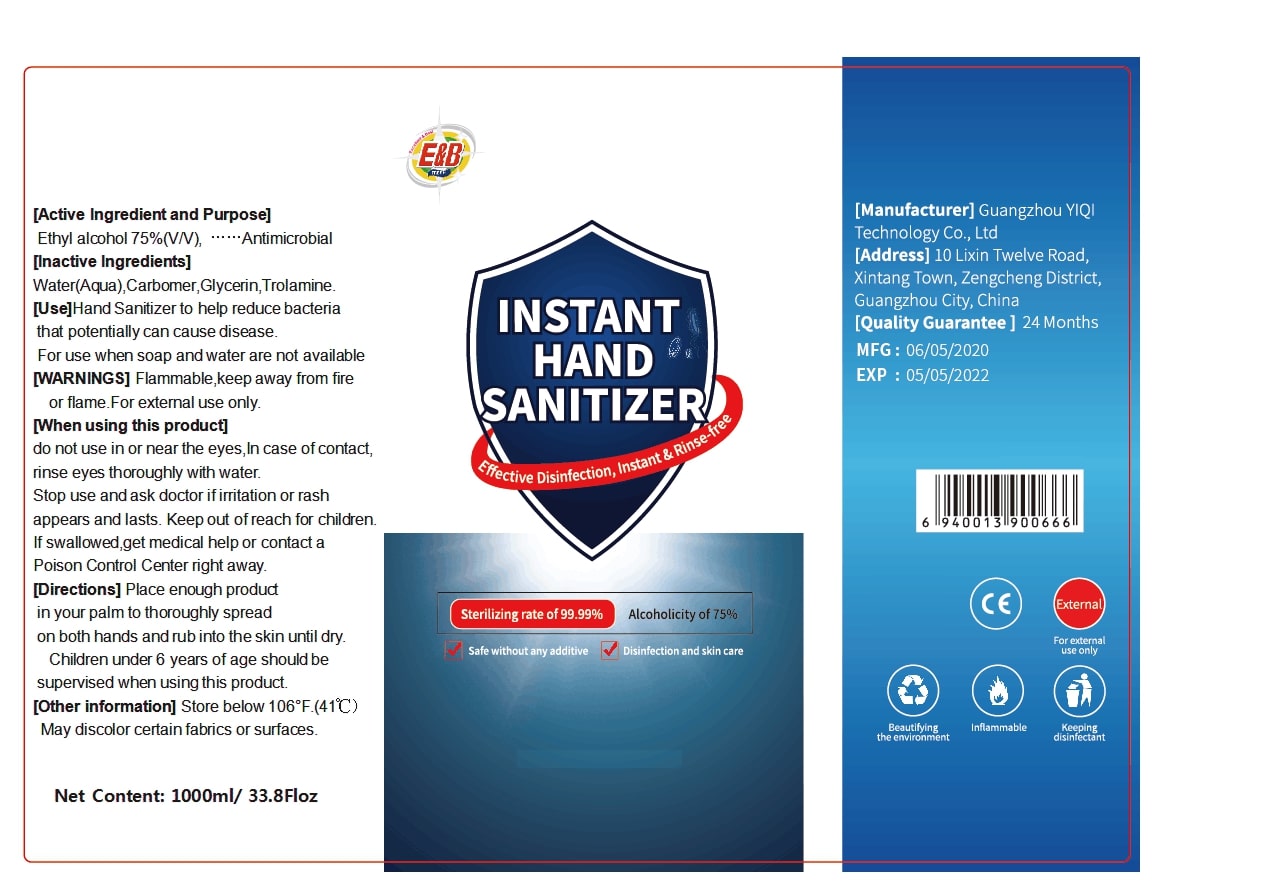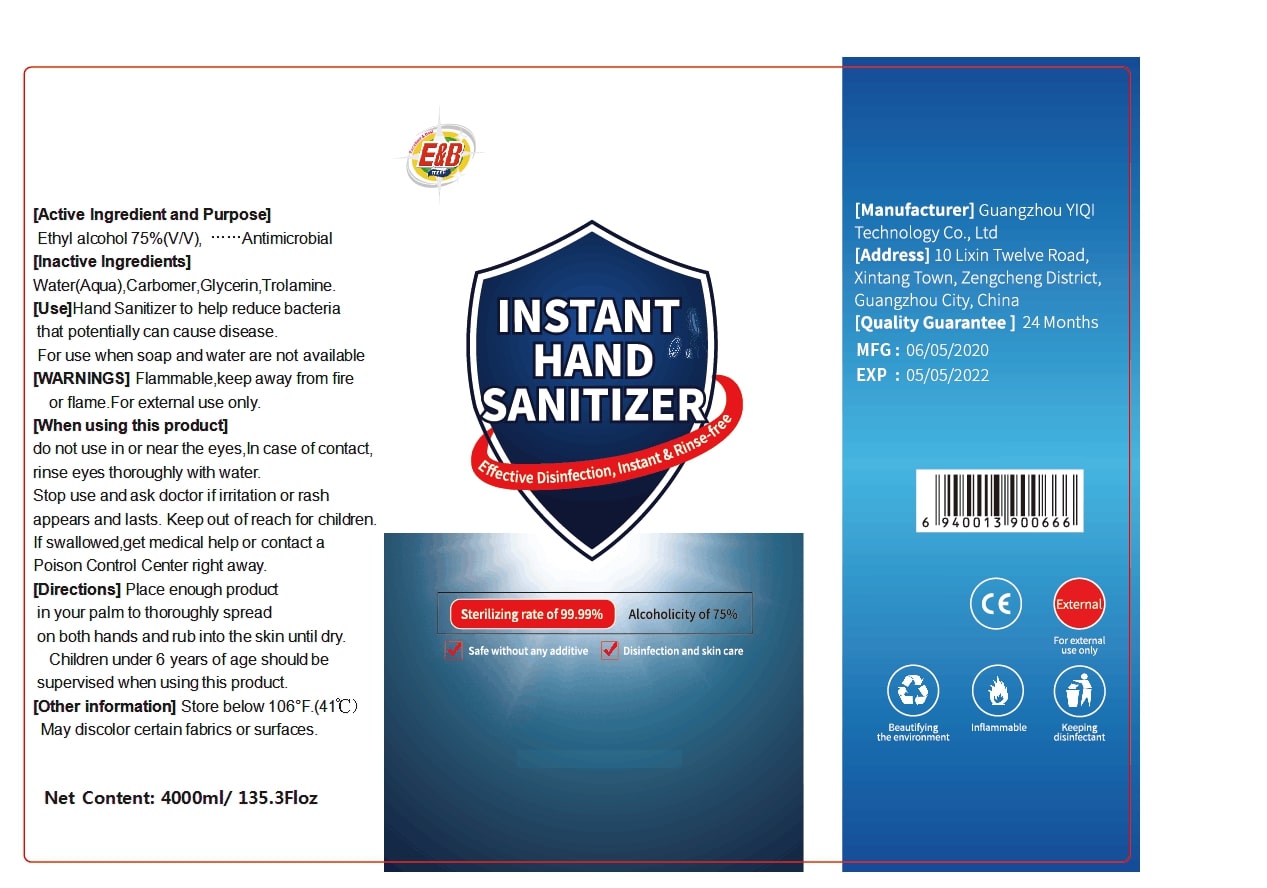 DRUG LABEL: Hand Sanitizer
NDC: 78295-003 | Form: GEL
Manufacturer: GUANGZHOU YIQI TECHNOLOGY CO.,LTD
Category: otc | Type: HUMAN OTC DRUG LABEL
Date: 20200518

ACTIVE INGREDIENTS: ALCOHOL 75 mL/100 mL
INACTIVE INGREDIENTS: CARBOMER HOMOPOLYMER, UNSPECIFIED TYPE; WATER; GLYCERIN; TROLAMINE

Hand Sanitizer

Active Ingredient

Ethyl alcohol 75%(V/V)

Purpose

Antimicrobial

Use

Hand Sanitizer to help reduce bacteria that potentially can cause disease.

For use when soap and water are not available

WARNINGS

Flammable,keep away from fire or flame.For external use only.

When using this product

do not use in or near the eyes, In case of contact, rinse eyes thoroughly with water.Stop use and ask doctor if irritation or rash

appears and lasts.Keep out of reach for children.If swallowed,get medical help or contact a Poison Control Center right away.

Directions

Place enough product in your palm to thoroughly spread on both hands and rub into the skin until dry.

Children under 6 years of age should be supervised when using this product.

Other information

Store below 106°F.(41℃)

May discolor certain fabrics or surfaces.

Inactive Ingredients

Water(Aqua) , Carbomer,Glycerin, Trolamine.